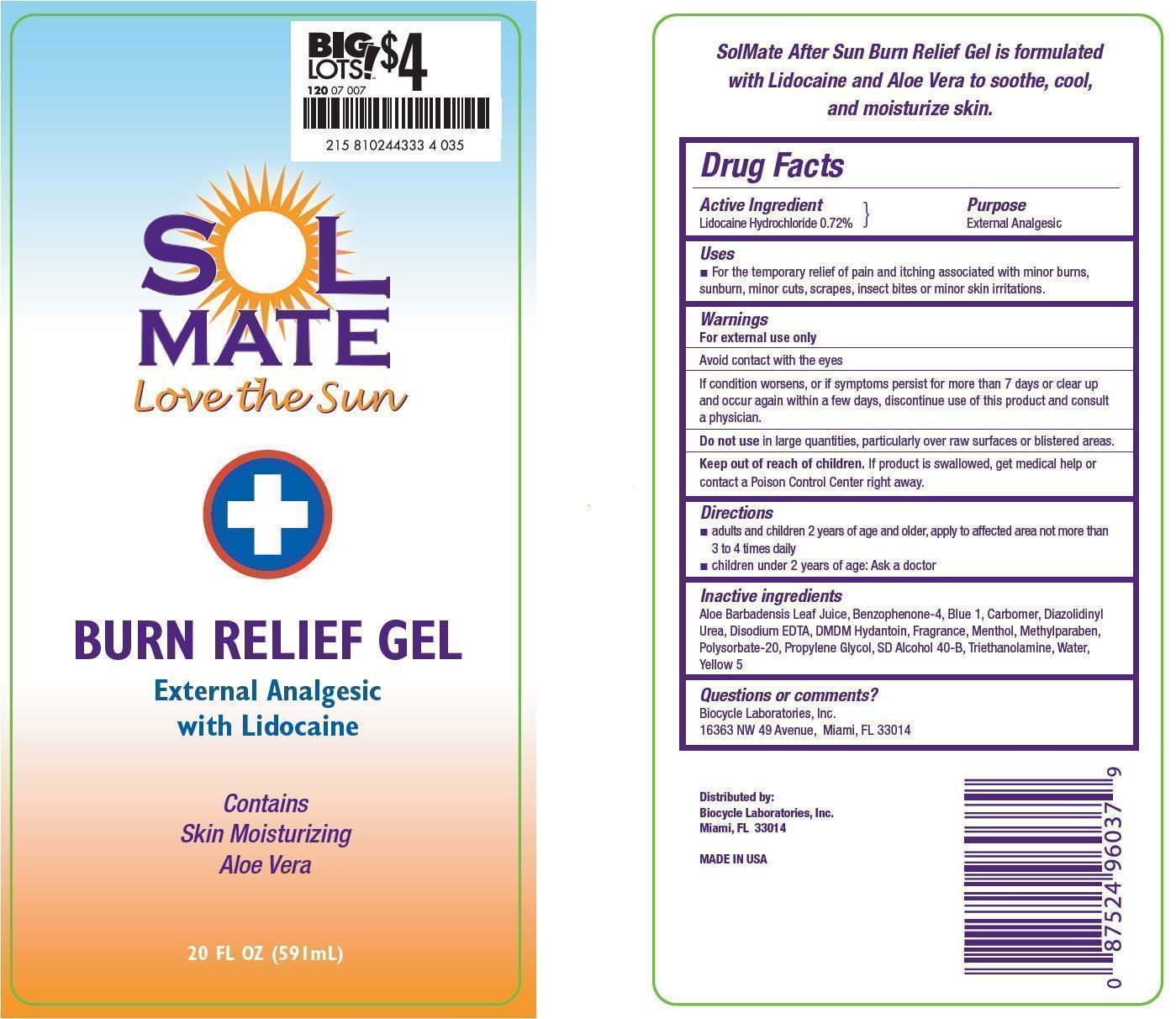 DRUG LABEL: Solmate
NDC: 58443-0145 | Form: GEL
Manufacturer: Prime Enterprises, Inc.
Category: otc | Type: HUMAN OTC DRUG LABEL
Date: 20150129

ACTIVE INGREDIENTS: LIDOCAINE 0.057 mg/1 mL
INACTIVE INGREDIENTS: ALOE VERA LEAF; BENZOPHENONE; FD&C BLUE NO. 1; CARBOMER HOMOPOLYMER TYPE C (ALLYL PENTAERYTHRITOL CROSSLINKED); DIAZOLIDINYL UREA; EDETATE DISODIUM; DMDM HYDANTOIN; MENTHOL; METHYLPARABEN; POLYSORBATE 20; PROPYLENE GLYCOL; ALCOHOL; TROLAMINE; WATER; FD&C YELLOW NO. 5

PRINCIPAL DISPLAY PANEL - 591 mL Bottle Label

SOL

MATE

LOVE THE SUN

BURN RELIEF GEL

External Analgesic

with Lidocaine

Contains

Skin Moisturizing

Aloe Vera

20 FL OZ (591 mL)

Active ingredients

Lidocaine Hydrochloride 0.72 %

Purpose

External Analgesic

Uses

For the temporary relief of pain and itching associated with minor burns, sunburn, minor cuts, scrapes, insect bites or minor skin irritations.

Warnings

OTHER SAFETY INFORMATION

For external use only

WHEN USING

- Avoid contact with the eyes.
- If condition worsens, or if symptoms persist for more than 7 days or clear up and occur again within a few days, discountinue use of this product and consult a physician.

Do not use in large quantities, particularly over raw surfaces or blistered areas.

Keep out of reach of children. If product is swallowed, get medical help or contact a Poison Control Center right away.

Directions

- Adults and children 2 years of age and older, apply to afftected area not more than 3 to 4 times daily.
- Children under 2 years of age: ask a doctor.

Inactive ingredients

Aloe Barbadensis Leaf Juice, Benzophenone-4, Blue 1, Carbomer, Diazolidinyl Urea, Disodium EDTA, DMDM Hydantoin, Fragrance, Menthol, Methylparaben, Polysorbate 20, Propylene Glycol, SD Alcohol 40-B, Triethanolamine, Water, Yellow 5

Questions or Comments?

Biocycle Laboratories, Inc.

16363 NW 49 Avenue, Miami, Fl 33014